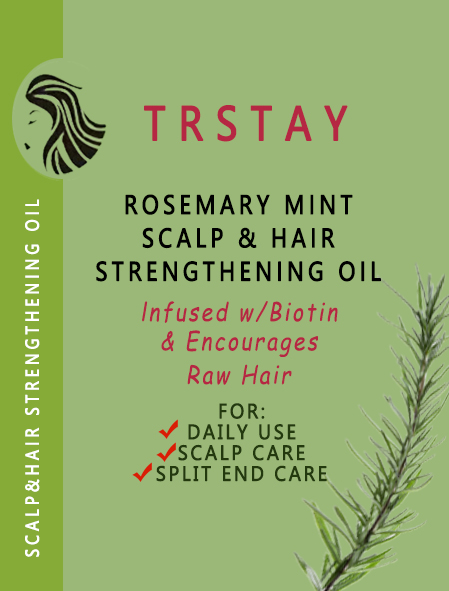 DRUG LABEL: Hair Strengthening Oil
NDC: 84515-250 | Form: LIQUID
Manufacturer: Yiwu Xinqian E Commerce Co Ltd
Category: otc | Type: HUMAN OTC DRUG LABEL
Date: 20241009

ACTIVE INGREDIENTS: MINOXIDIL 5 g/100 mL
INACTIVE INGREDIENTS: CHLORPHENESIN; SESAME OIL; GLYCERIN; PALMITOYL TRIPEPTIDE-1; PALMITOYL TETRAPEPTIDE-7

INACTIVE INGREDIENT

Acrylates copolymer, Ethyl acetate

KEEP OUT OF REACH OF CHILDREN

If sxralowed, get medical help or contact a Poison Conirol Cenler ngiht away.

STOP USE

on broken or irritated scalp

When using this product, avoid contact with eyes. lf contact occurs, rinse thoroughly with waterDiscontinue use if any irritation or adverse reaction occurs.

DO NOT USE

Discontinue use if any irritation or adverse reaction occurs

DOSAGE AND ADMINISTRATION

For external use only.

INDICATIONS AND USAGE

Apply twice daly(moring and night as a man and once as a woman.Afer apicaion, proeed with an acive masage for 3-5 minutes unthe product is fuy absorbed

PURPOSE

wart remover

COMPONENTS

Salicylic acid 2%